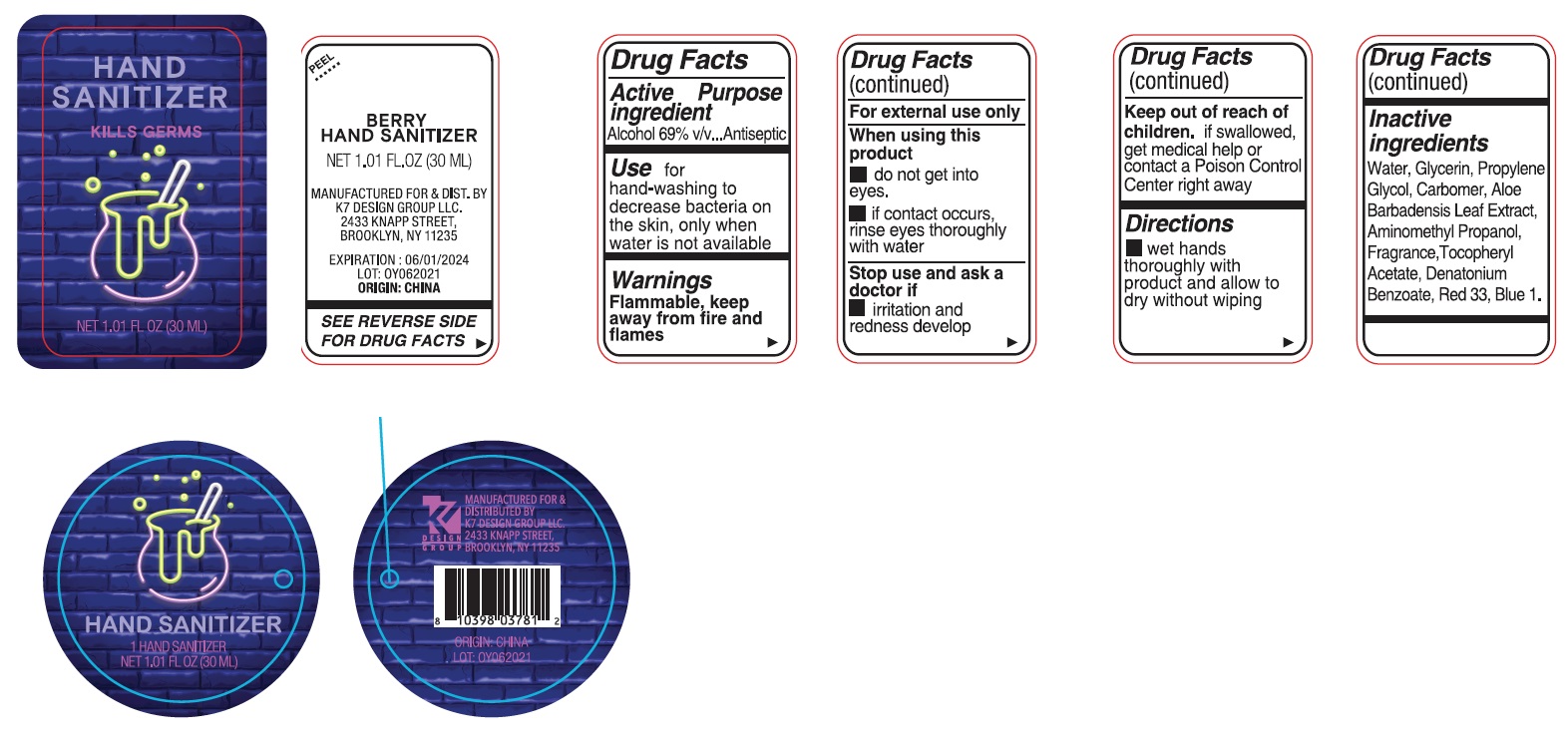 DRUG LABEL: Berry Hand Sanitizer
NDC: 74177-993 | Form: GEL
Manufacturer: K7 Design Group Inc.
Category: otc | Type: HUMAN OTC DRUG LABEL
Date: 20210601

ACTIVE INGREDIENTS: ALCOHOL 69 mL/100 mL
INACTIVE INGREDIENTS: ALOE VERA LEAF; AMINOMETHYLPROPANOL; WATER; CARBOMER HOMOPOLYMER, UNSPECIFIED TYPE; DENATONIUM BENZOATE; GLYCERIN; PROPYLENE GLYCOL; .ALPHA.-TOCOPHEROL ACETATE; D&C RED NO. 33; FD&C BLUE NO. 1

Berry Hand Sanitizer

Active ingredient

Alcohol 69% v/v

Purpose

Antiseptic

Use

for hand-washing to decrease bacteria on the skin, only when water is not available

Warnings

Flammable, keep away from fire and flames

For external use only

When using this product

- do not get into eyes.
- if contact occurs, rinse eyes thoroughly with water

Stop use and ask a doctor if

- irritation and redness develop

Keep out of reach of children.

if swallowed, get medical help or contact a Poison Control Center right away

Directions

- wet hands thoroughly with product and allow to dry without wiping

Inactive ingredients

Water, Glycerin, Propylene Glycol, Carbomer, Aloe Barbadensis Leaf Extract, Aminomethyl Propanol, Fragrance, Tocopheryl Acetate, Denatonium Benzoate, Red 33, Blue 1.

Company Information

MANUFACTURED FOR & DIST. BY K7 DESIGN GROUP LLC

2344 KNAPP STREET

BROOKLYN, NY 11235